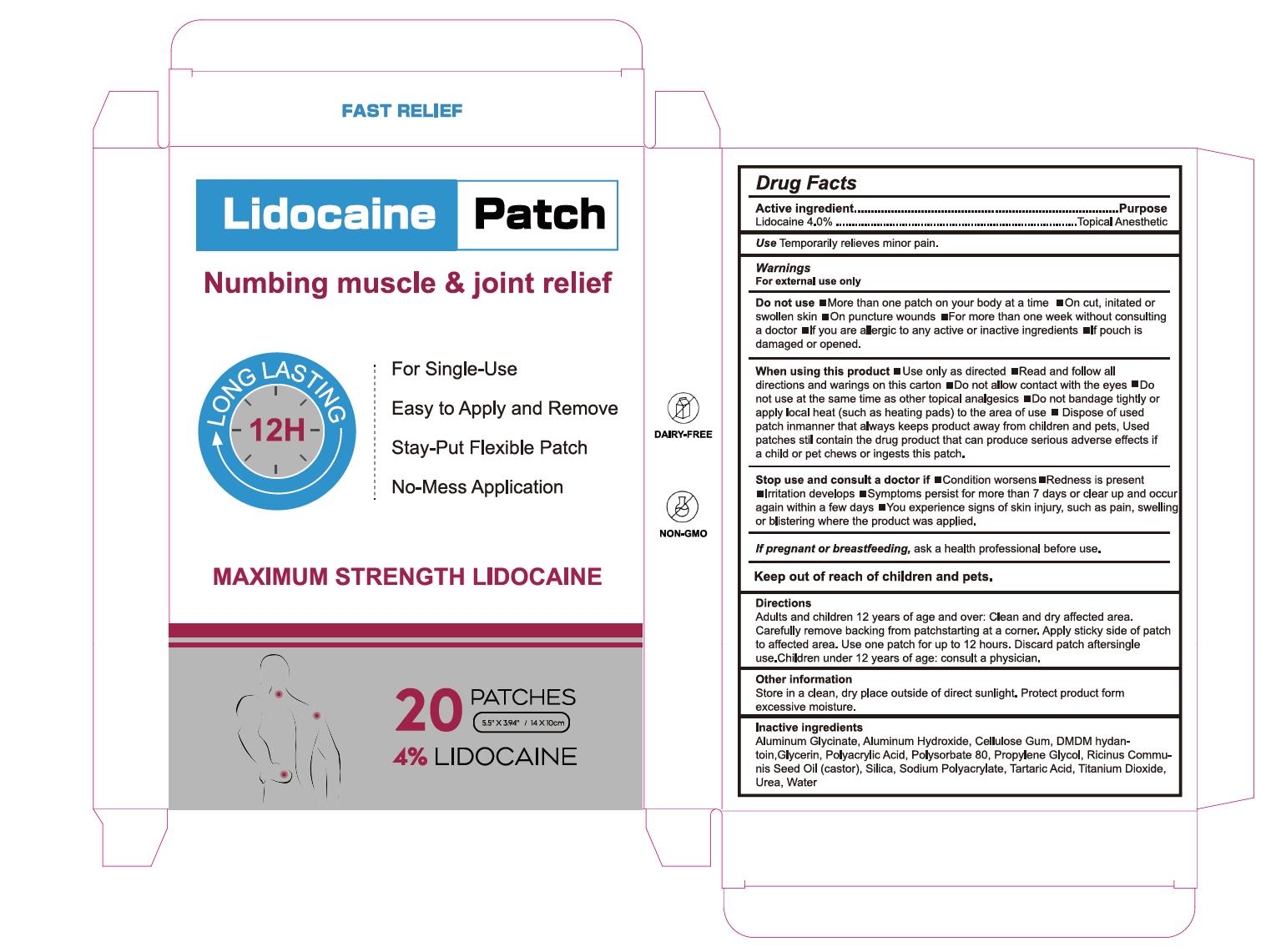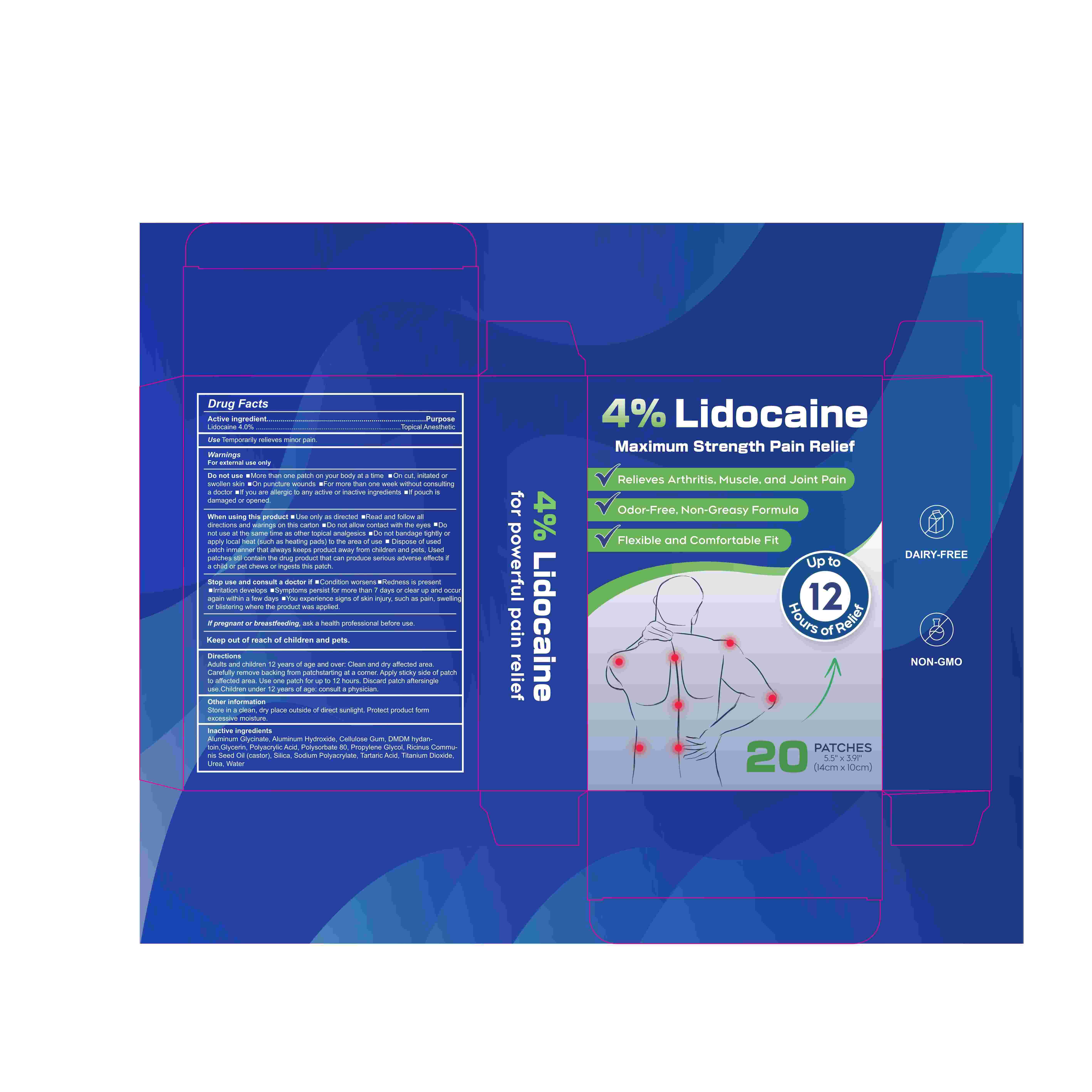 DRUG LABEL: Lidocaine Patch
NDC: 84023-601 | Form: PATCH
Manufacturer: Shenzhen Yangan Technology Co., Ltd.
Category: otc | Type: HUMAN OTC DRUG LABEL
Date: 20241122

ACTIVE INGREDIENTS: LIDOCAINE 4 g/100 g
INACTIVE INGREDIENTS: SILICON DIOXIDE; ALUMINUM HYDROXIDE; POLYACRYLIC ACID (250000 MW); CASTOR OIL; DMDM HYDANTOIN; GLYCERIN; PROPYLENE GLYCOL; TITANIUM DIOXIDE; POLYSORBATE 80; WATER; SODIUM POLYACRYLATE (8000 MW); TARTARIC ACID; UREA; DIHYDROXYALUMINUM AMINOACETATE ANHYDROUS; CARBOXYMETHYLCELLULOSE SODIUM, UNSPECIFIED FORM

Lidocaine Patch

Lidocaine Patch

ACTIVE INGREDIENT

Lidocaine 4%

PURPOSE

Topical Anesthetic

INDICATIONS AND USAGE

Temporarily relieves minor pain.

WARNINGS

For external use only

DO NOT USE

More than one patch on your body at a time
On cut, initated or swollen skin
On puncture wounds
For more than one week without consulting a doctor
lf you are allergic to any active or inactive ingredients lf pouch is damaged or opened.

When using this product Use only as directed Read and follow alldirections and warings on this carton Do not allow contact with the eyes
Do not use at the same time as other topical analgesics
Do not bandage tightly orapply local heat (such as heating pads) to the area of use
Dispose of usedpatch inmanner that always keeps product away from children and pets, Used patches stil contain the drug product that can produce serious adverse effects ifa child or pet chews or ingests this patch.

Stop use and consult a doctor if
Condition worsens
Redness is present
Irritation develops
Symptoms persist for more than 7 days or clear up and occur again within a few days
You experience signs of skin injury, such as pain, swelling or blistering where the product was applied.

Keep out of reach of children and pets

DOSAGE AND ADMINISTRATION

Adults and children 12 years of age and over: Clean and dry affected area.Carefully remove backing from patchstarting at a corner. Apply sticky side of patchto affected area. Use one patch for up to 12 hours. Discard patch aftersingleuse.Children under 12 years of age: consult a physician.

STORAGE AND HANDLING

Store in a clean, dry place outside of direct sunlight. Protect product form
excessive moisture.

INACTIVE INGREDIENT

Aluminum Glycinate
Aluminum Hydroxide
Cellulose Gum
DMDM hydantoin
Glycerin

Polyacrylic Acid
Polysorbate 80
Propylene Glycol
Ricinus Communis Seed Oil (castor)
Silica
Sodium Polyacrylate
Tartaric Acid
Titanium Dioxide
Urea
Water